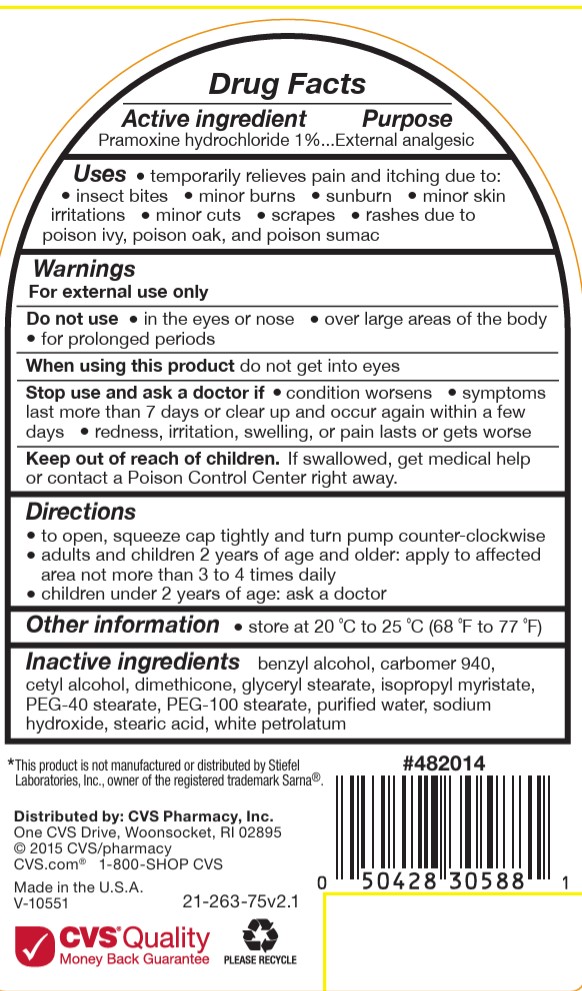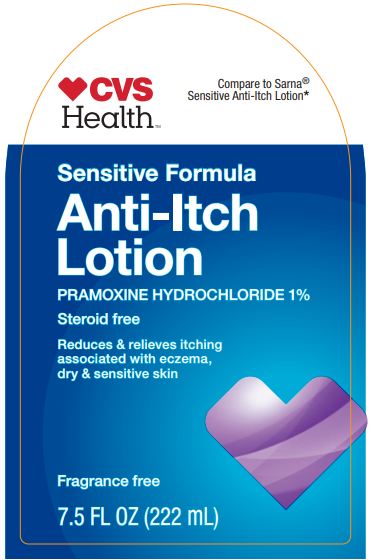 DRUG LABEL: CVS Anti-Itch
NDC: 69842-263 | Form: LOTION
Manufacturer: CVS
Category: otc | Type: HUMAN OTC DRUG LABEL
Date: 20251119

ACTIVE INGREDIENTS: PRAMOXINE HYDROCHLORIDE 1 g/100 g
INACTIVE INGREDIENTS: ISOPROPYL MYRISTATE; WATER; PEG-40 STEARATE; CETYL ALCOHOL; STEARIC ACID; SODIUM HYDROXIDE; CARBOMER 940; PETROLATUM; GLYCERYL STEARATE/PEG-100 STEARATE; DIMETHICONE 350; BENZYL ALCOHOL

CVS Sensitivel Anti-Itch Lotion

Active Ingredients

Pramoxine HCl 1% External analgesic

Uses

temporary relieves pain and itching due to:

insect bites

minor burns

sunburn

minor skin irritations

minor cuts

scrapes

rashes due to poison ivy, poison oak, and poison sumac

dries the oozing and weeping of poison:

ivy

oak

sumac

Warning

For external use only

Do not use

in the eyes or nose

over large areas of the body

for prolonged periods

ASk doctor before use

on chicken pox

on measles

when using this product

do not get into eyes

Stop Use and ask doctor if

condition worsens

symptoms last more than 7 days or clear up and occur again within a few days

Keep out of reach of children

If swallowed, get medical help or contact a Poison Control Center right away.

Purpose

Anti - itch

Directions

to open, squeeze cap tightly and turn pump counter-clockwise

adults and children 2 years and older: apply to affected area not more than 3 to 4 times daily

children under 2 years: ask a doctor

Other information

store at 20 °C to 25 °C (68 °F to 77 °F)

Inactive ingredients

benzyl alcohol, carbomer 940, cetyl alcohol, dimethicone, glyceryl stearate, isopropyl myristate, PEG-40 stearate,
PEG-100 stearate, purified water, sodium hydroxide, stearic acid, white petrolatum

PACKAGE LABEL

CVS Health

Compare to Sarna Sensitive Anti-Itch Lotion

Sensitive Formula Anti-Itch Lotion

Pramoxine Hydrochloride 1 percent

Steroid Free

Reduces and Relieves Itching associated with eczema, dry and sensitive skin